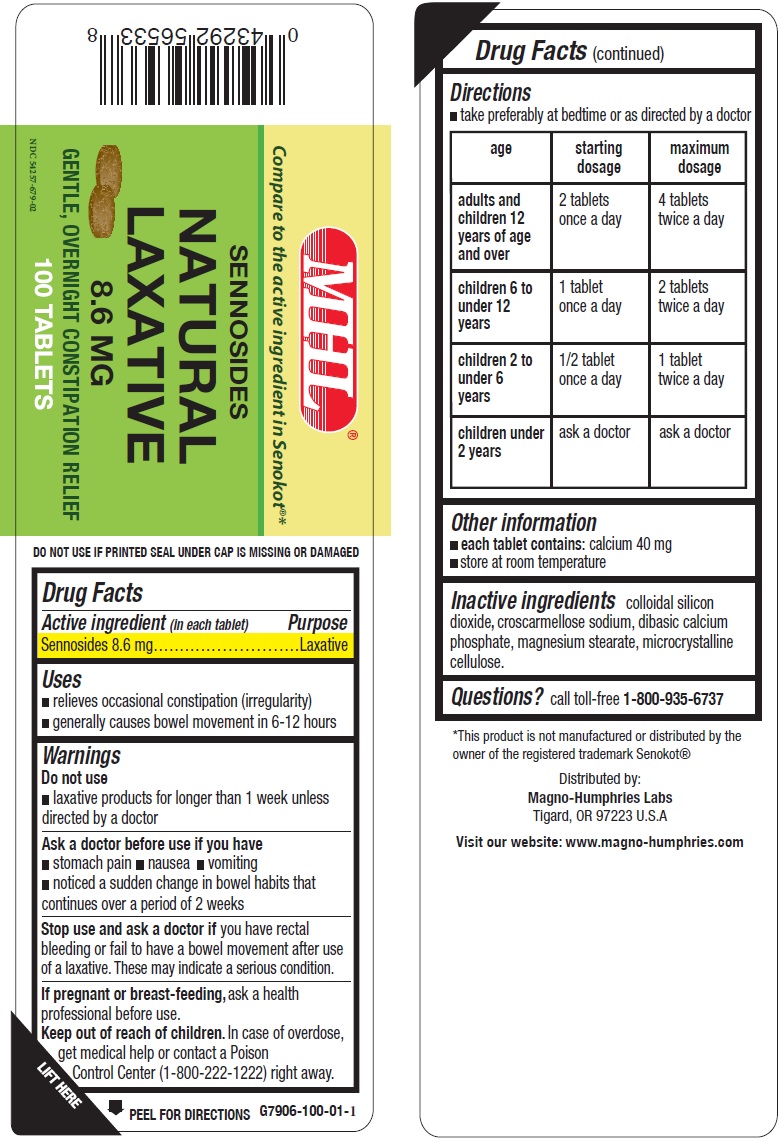 DRUG LABEL: Sennosides Natural Laxative
NDC: 54257-679 | Form: TABLET
Manufacturer: Magno-Humphries, Inc.
Category: otc | Type: HUMAN OTC DRUG LABEL
Date: 20231027

ACTIVE INGREDIENTS: SENNOSIDES 8.6 mg/1 1
INACTIVE INGREDIENTS: SILICON DIOXIDE; CROSCARMELLOSE SODIUM; ANHYDROUS DIBASIC CALCIUM PHOSPHATE; MAGNESIUM STEARATE; MICROCRYSTALLINE CELLULOSE

Sennosides Natural Laxative

Active ingredient (in each tablet))

Sennosides 8.6 mg

Purpose

Laxative

Uses

- relieves occasional constipation (irregularity)
- generally causes bowel movement in 6-12 hours

Warnings

Do not use

- laxative products for longer than 1 week unless directed by a doctor

Ask a doctor before use if you have

- stomach pain
- nausea
- vomiting
- noticed a sudden change in bowel habits that continues over a period of 2 weeks

Stop use and ask a doctor if

you have rectal bleeding or fail to have a bowel movement after use of a laxative. These may indicate a serious condition.

If pregnant or breast-feeding,

ask a health professional before use.

Keep out of reach of children.

In case of overdose, get medical help or contact a Poison Control Center (1-800-222-1222) right away.

Directions

- take preferably at bedtime or as directed by a doctor

age | starting dosage | maximum dosage
adults and children 12 years of age and over | 2 tablets once a day | 4 tablets twice a day
children 6 to under 12 years | 1 tablet once a day | 2 tablets twice a day
children 2 to under 6 years | 1/2 tablet once a day | 1 tablet twice a day
children under 2 years | ask a doctor | ask a doctor

Other information

- each tablet contains: calcium 40mg
- store at room temperature

Inactive ingredients

colloidal silicon dioxide, croscarmellose sodium, dibasic calcium phosphate, magnesium stearate, microcrystalline cellulose.

Questions?

call toll-free 1-800-935-6737